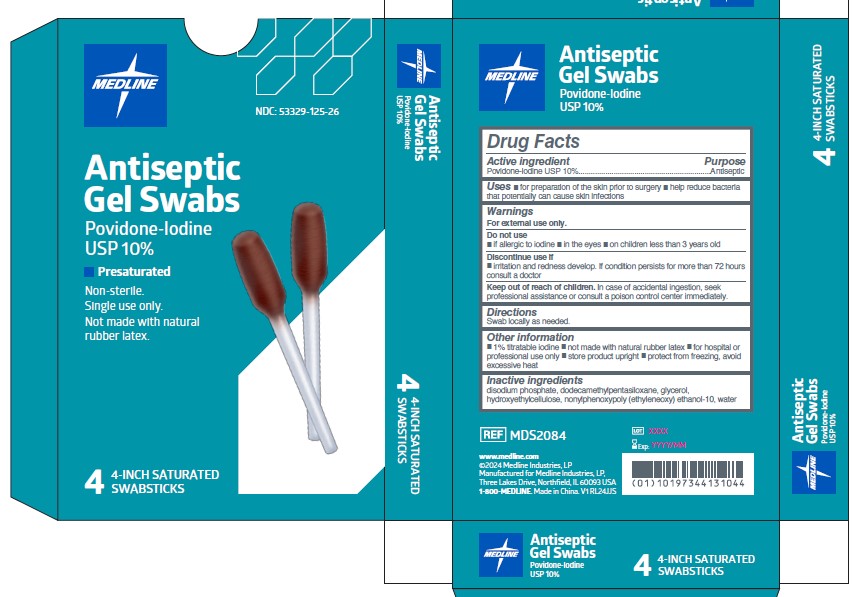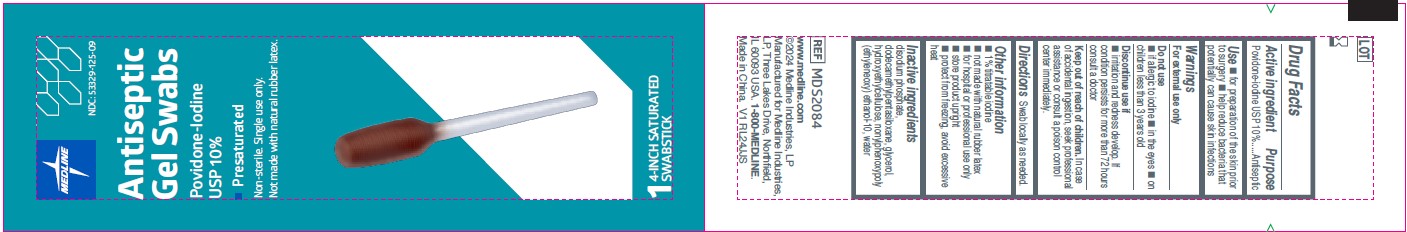 DRUG LABEL: Medline
NDC: 53329-125 | Form: SWAB
Manufacturer: Medline Industries, LP
Category: otc | Type: HUMAN OTC DRUG LABEL
Date: 20251009

ACTIVE INGREDIENTS: POVIDONE-IODINE 10 mg/1 mL
INACTIVE INGREDIENTS: GLYCERIN; NONOXYNOL-2; HYDROXYETHYL CELLULOSE, UNSPECIFIED; WATER; SODIUM PHOSPHATE, DIBASIC, ANHYDROUS; DODECAMETHYLPENTASILOXANE

125 Medline PVP-I Gel Swabstick

Active Ingredient

Povidone-iodine USP 10%

Purpose

Antiseptic

Uses

- for preparation of the skin prior to surgery
- helps reduce bacteria that potentially can cause skin infection

Warnings

For external use only

Do not use

- if allergic to iodine
- in the eyes
- on children less than 3 years old

Discontinue use if

- irritation and redness develop. If condition persists for more than 72 hours consult a doctor

Keep out of reach of children.

In case of accidental ingestion, seek professional assistance or consult a poison control center immediately.

Directions

swab locally as needed

Other Information

- 1% titratable iodine
- not made with natural rubber latex
- for hospital or professional use only
- store product upright
- protect from freezing, avoid excessive heat

Inactive ingredients

disodium phosphate, dodecamethylpentasiloxane, glycerol, hydroxyethylcellulose, nonylphenoxypoly (ethyleneoxy) ethanol-10, water

Manufacturing information

www.medline.com

©2024 Medline Industries, LP

Manufactured for Medline Industries, LP, Three Lakes Drive, Northfield, IL 60093 USA

1-800-MEDLINE

Made in China.

major change section

Update made to Uses and Directions